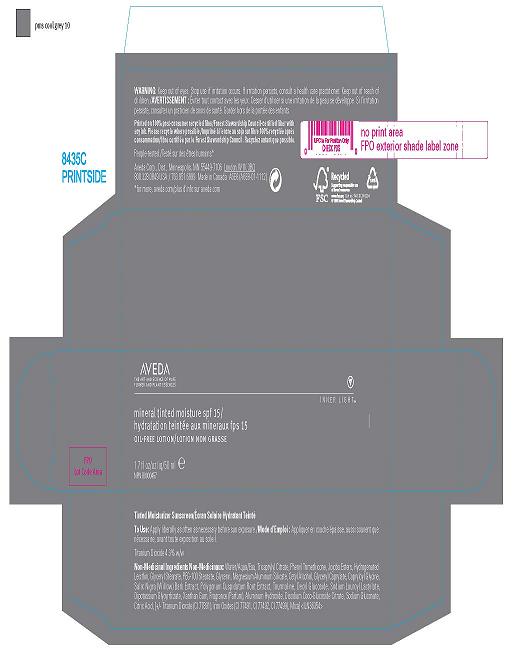 DRUG LABEL: MINERAL TINTED MOISTURIZER 
NDC: 57677-057 | Form: LOTION
Manufacturer: Aveda Corporation
Category: otc | Type: HUMAN OTC DRUG LABEL
Date: 20100330

ACTIVE INGREDIENTS: TITANIUM DIOXIDE 4.30 mL/100 mL

WARNINGS AND PRECAUTIONS

MINERAL TINTED MOISTURIZER SPF 15
OIL FREE LOTION
1.7 FL . OZ/ 50 ML
AVEDA CORPORATION DISTR.
MINNEAPOLIS, MN 54499 7106
ACTIVE INGREDIENT: TITANIUM DIOXIDE, 4.3%
TO USE: APPLY LIBERALLY AS OFTEN AS POSSIBLE BEFORE SUN EXPOSURE
WARNING: KEEP OUT OF EYES. STOP USE IF IRRITATION OCCURS. IF IRRITATION PERSISTS CONSULT A HEALTH CARE PRACTITIONER. KEEP OUT OF REACH OF CHILDREN.